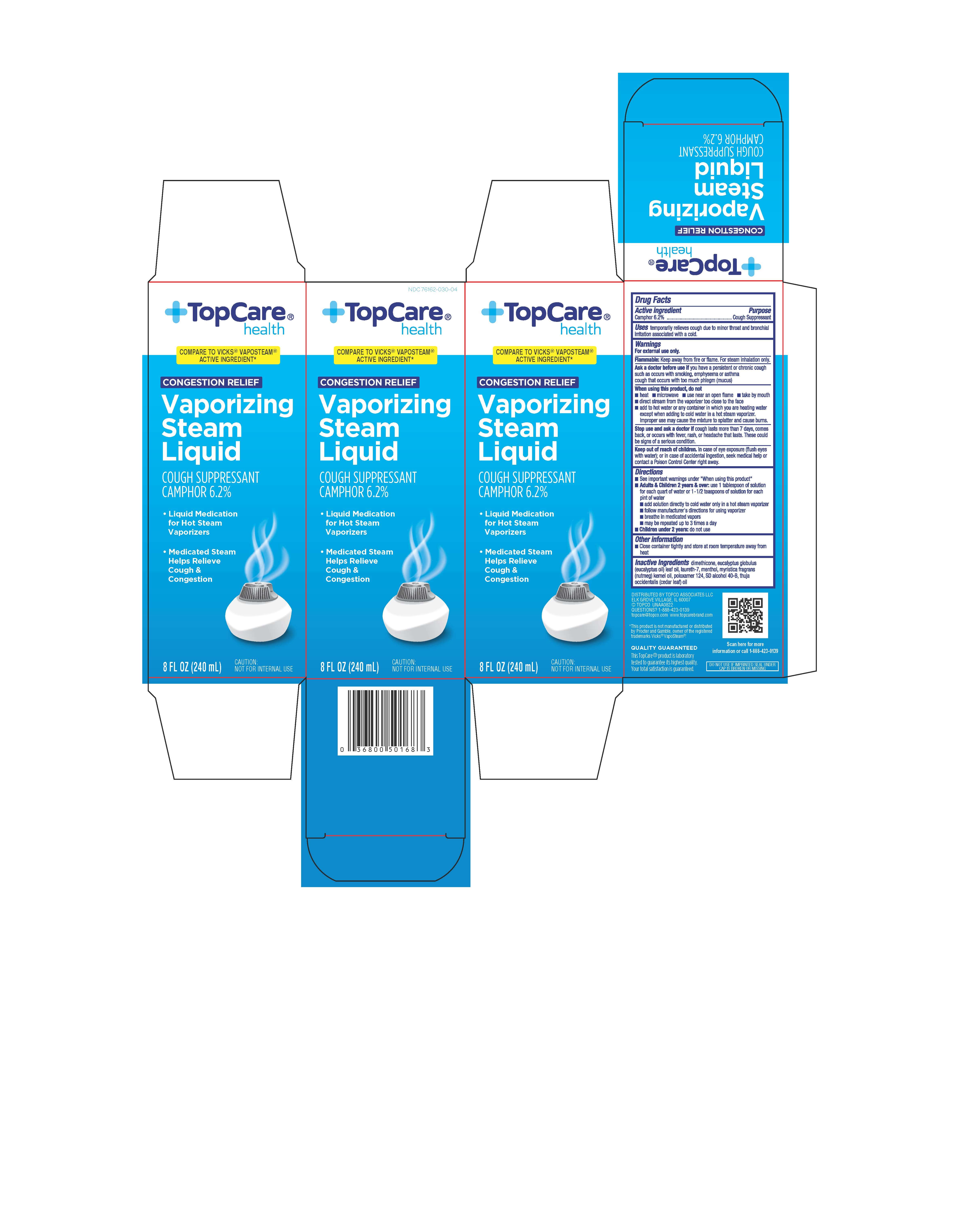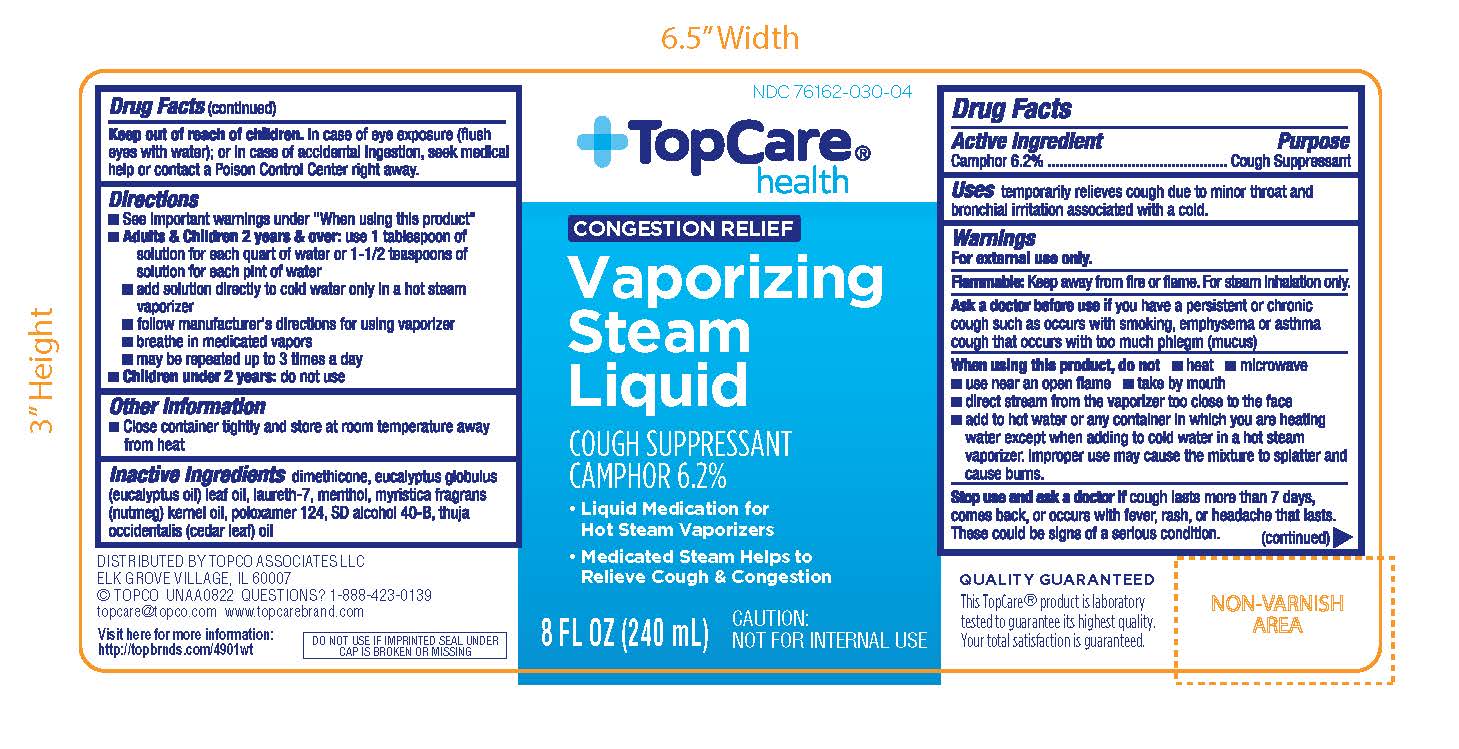 DRUG LABEL: Vapo Steam
NDC: 76162-030 | Form: LIQUID
Manufacturer: TOPCO ASSOCIATES, LLC
Category: otc | Type: HUMAN OTC DRUG LABEL
Date: 20260114

ACTIVE INGREDIENTS: CAMPHOR (SYNTHETIC) 6.2 g/100 mL
INACTIVE INGREDIENTS: ALCOHOL; EUCALYPTUS OIL; NUTMEG OIL; DIMETHICONE; CEDAR LEAF OIL; MENTHOL; LAURETH-7

TopCare®Health Vaporizing Steam Liquid 8 FL OZ (240 mL)

Active ingredient

Camphor (Synthetic) 6.2%

Purpose

Cough suppressant

Uses

temporarily relieves cough due to minor throat and bronchial irritation associated with a cold.

Warnings

For external use only.

Flammable:Keep away from fire or flame. For steam inhalation only.

Ask a doctor before use if you have

- a persistent or chronic cough such as occurs with smoking, asthma or emphysema
- cough that occurs with too much phlegm (mucus)

When using this product, do not

- heat
- microwave
- use near an open flame
- direct steam from the vaporizer too close to the face
- add to hot water or any container where heating water except when adding to cold water only in a hot steam vaporizer. May cause splattering and result in burns.

Stop use and ask a doctor if

cough lasts more than 7 days, comes back, or occurs with fever, rash, or headache that lasts. These could be signs of serious condition.

Keep out of reach of children.

In case of eye exposure (flush eyes with water); or in case of accidental igestion, seek medical help or contact a Poison Control Center right away.

Directions

- see important warnings under "When using this product"
- adults & children 2 years & over:

add 1 tablespoon of solution to each quart of water or 1½ teaspoons of solution to each pint of water

add solution directly to cold water only in a hot steam vaporizer

follow manufacturer's directions for using vaporizer

breathe in the medicated vapors

use up to three times daily or as directed by a doctor

- children under 2 years: do not use

Other information

- close container tightly and store at room temperature away from heat

Inactive ingredients

dimenthicone, eucalyptus globulus (eucalyptus oil) leaf oil, laureth-7, menthol, myristica fragrans (nutmeg) kernel oil, poloxamer 124, SD alcohol 40-B, thuja occidentalis (cedar leaf) oil